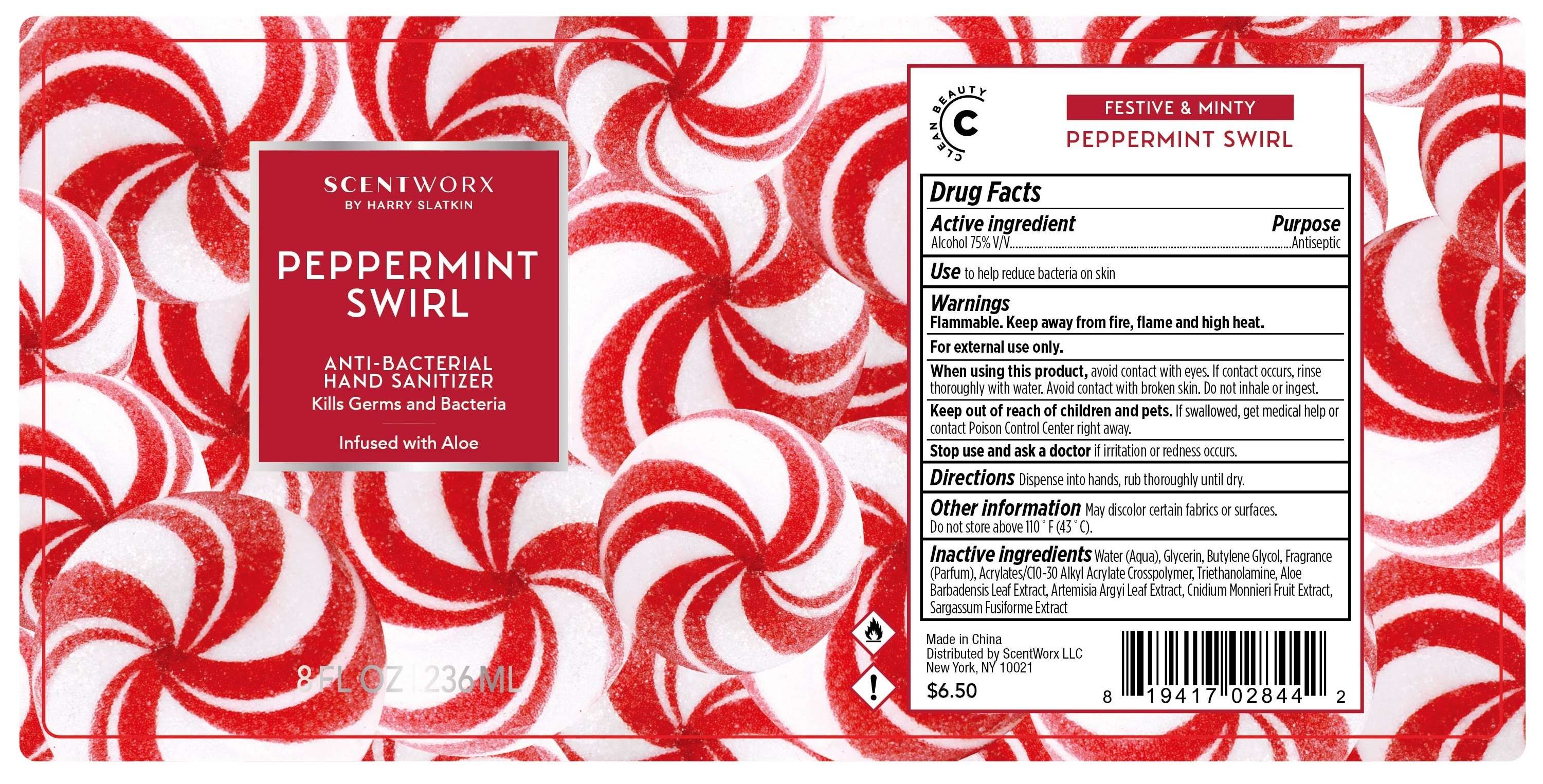 DRUG LABEL: Hand Sanitizer
NDC: 81282-044 | Form: GEL
Manufacturer: HS HomeWorx LLC
Category: otc | Type: HUMAN OTC DRUG LABEL
Date: 20210518

ACTIVE INGREDIENTS: ALCOHOL 75 mL/100 mL
INACTIVE INGREDIENTS: GLYCERIN 1 mL/100 mL; WATER 22 mL/100 mL; BUTYLENE GLYCOL 1 mL/100 mL

This is a hand sanitizer manufactured according to the Temporary Policy for Preparation of Certain Alcohol-Based Hand Sanitizer Products During the Public Health Emergency (CoViD-19); Guidance for Industry.

The hand sanitizer is manufactured using only the following United States Pharmacopoeia (USP) grade ingredients in the preparation of the product (percentage in final product formulation) consistent with World Health Organization (WHO) recommendations:

1. Alcohol (ethanol) (USP or Food Chemical Codex (FCC) grade) (80%, volume/volume (v/v)) in an aqueous solution denatured according to Alcohol and Tobacco Tax and Trade Bureau regulations in 27 CFR part 20.
2. Glycerol (1.45% v/v).
3. Hydrogen peroxide (0.125% v/v).
4. Sterile distilled water or boiled cold water.

The firm does not add other active or inactive ingredients. Different or additional ingredients may impact the quality and potency of the product.

Active Ingredient(s)

Alcohol 75% v/v. Purpose: Antiseptic

Purpose

Antiseptic, Hand Sanitizer

Use

to help reduce bacteria on skin

Warnings

Flammable. Keep away from fire, flame or high heat.

For external use only.

Do not use

- in children less than 2 months of age
- on open skin wounds

When using this product avoid contact with eyes. If contact occurs, rinse thoroughly with water.
Avoid contact with broken skin. Do no inhale or ingest.

Stop use and ask a doctor if irritation or redness occurs.
Keep out of reach of children and pets. If swallowed, get medical help or contact a Poison Control Center right away.

Stop use and ask a doctor if irritation or rash occurs. These may be signs of a serious condition.

Keep out of reach of children. If swallowed, get medical help or contact a Poison Control Center right away.

Directions

- Dispense into hands, rub thoroughly until dry.

Other information

- Do not store above 110F (43C)
- May discolor certain fabriocs or surfaces.

Inactive ingredients

water (aqua), glycerin, butylene glycol, fragrance (parfum), acrylates/C10-30 alkyl acrylate crosspolymer, triethanolamine, aloe barbadensis leaf extract, artemisia argyi leaf extract, cnidium monnieri fruit extract, sargassum fusiforme extract

Package Label - Principal Display Panel

236 mL NDC: 81282-044-01